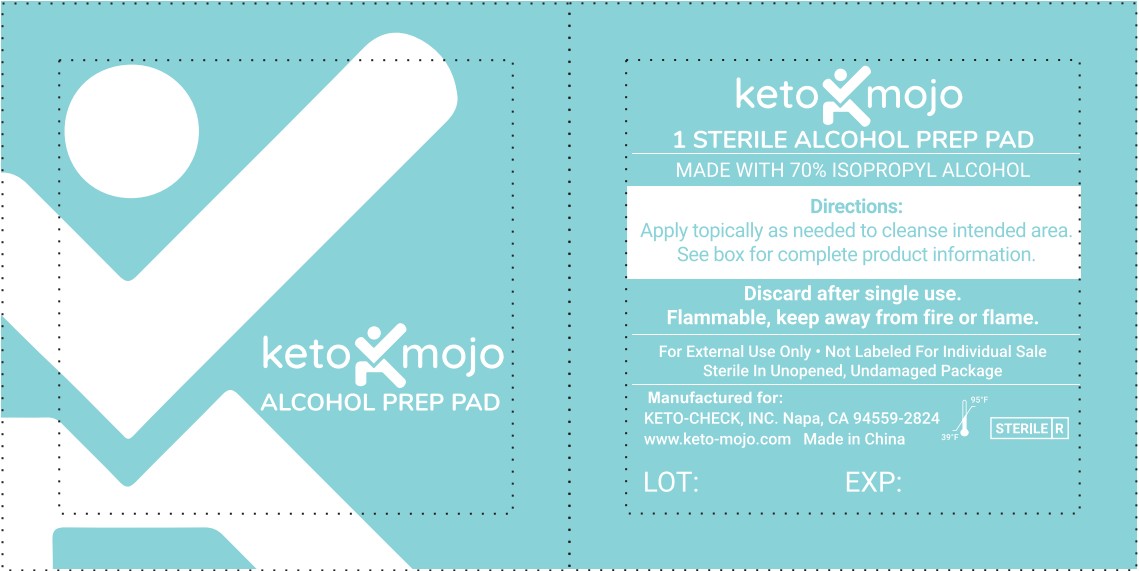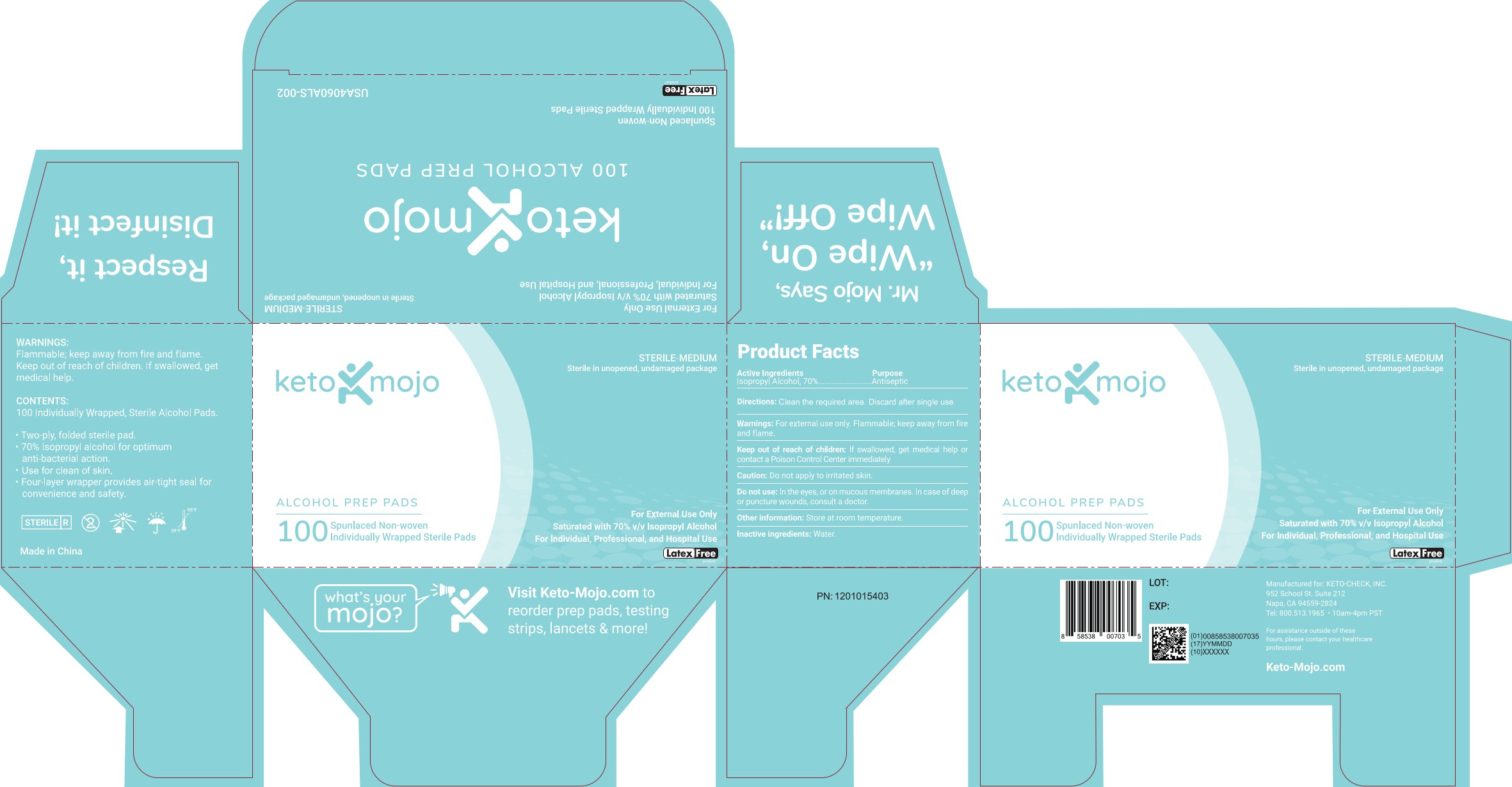 DRUG LABEL: Alcohol Prep Pads
NDC: 81849-003 | Form: CLOTH
Manufacturer: Shandong Lianfa Medical Plastic Products CO.,LTD
Category: otc | Type: HUMAN OTC DRUG LABEL
Date: 20251113

ACTIVE INGREDIENTS: ISOPROPYL ALCOHOL 70 mL/100 mL
INACTIVE INGREDIENTS: WATER

Pads, Isopropyl 70% v/v, 100pouch/box

Active Ingredients

Isopropyl Alcohol, 70% v/v. Purpose: Antiseptic

Purpose

Antiseptic

INDICATIONS AND USAGE

Use for clean of skin.

Warnings

For external use only. Flammable; keep away from fire or flame.

Do not use

In the eyes, or on mucous membranes. In case of deep or puncture wounds, consult a doctor.

Caution

Do not apply to irritated skin.

Keep out of reach of children.

If swallowed, get medical help or contact a Poison Control Center immediately

Directions

Clean the required area. Discard after single use.

Other information

Store at room temperature.

Inactive ingredients

Water